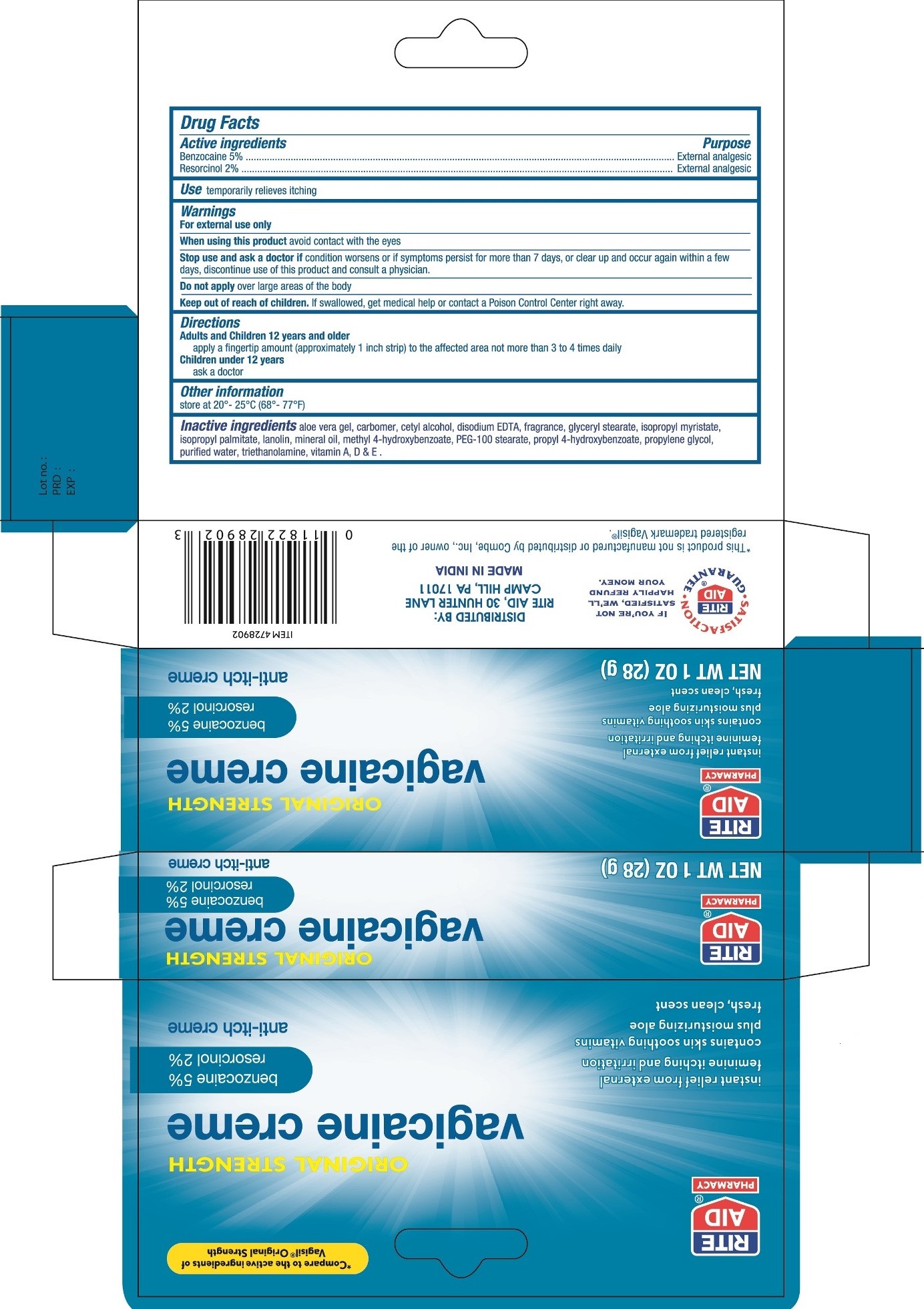 DRUG LABEL: Rite Aid Original Strength Vagicaine
NDC: 11822-9974 | Form: CREAM
Manufacturer: Rite Aid Corporation
Category: otc | Type: HUMAN OTC DRUG LABEL
Date: 20220131

ACTIVE INGREDIENTS: BENZOCAINE 5 g/100 g; RESORCINOL 2 g/100 g
INACTIVE INGREDIENTS: ALOE VERA LEAF; CARBOXYPOLYMETHYLENE; CETYL ALCOHOL; EDETATE DISODIUM; GLYCERYL MONOSTEARATE; ISOPROPYL MYRISTATE; ISOPROPYL PALMITATE; LANOLIN; MINERAL OIL; METHYLPARABEN; PEG-100 STEARATE; PROPYLPARABEN; PROPYLENE GLYCOL; WATER; TROLAMINE; VITAMIN A; VITAMIN D; .ALPHA.-TOCOPHEROL

Rite Aid Original Strength Vagicaine

Active ingredients

Benzocaine 5%

Resorcinol 2%

Purpose

External analgesic

Use

temporarily relieves itching

Warnings
For external use only.

When using this product avoid contact with the eyes.

Stop use and ask a doctor if condition worsens or if symptoms persist for more than 7 days, or clear up and occur again within a few days, discontinue use of this product and consult a physician.

Do not apply over large areas of the body.

KEEP OUT OF REACH OF CHILDREN

Keep out of the reach of children. If swallowed get medical help or contact a Poison Control Center right away.

Directions
Adults and Children 12 years and older
apply a fingertip amount (approximately 1 inch strip) to the affected area not more than 3 or 4 times daily.
Children under 12 years
ask a doctor

Other information

Store at 20° - 25 °C (68° - 77°F)

Inactive Ingredients

aloe vera gel, carbomer, cetyl alcohol, disodium EDTA, fragrance, glyceryl stearate, isopropyl myristate, isopropyl palmitate, lanolin, mineral oil, methyl 4-hydroxybenzoate, PEG-100 stearate, propyl 4-hydroxybenzoate, propylene glycol, purified water, triethanolamine, vitamin A, D & E.

PACKAGE LABEL

PRINCIPAL DISPLAY PANEL

RITE AID ORIGINAL STRENGTH VAGICAINE CREAM

NET WT 1 OZ (28 g)